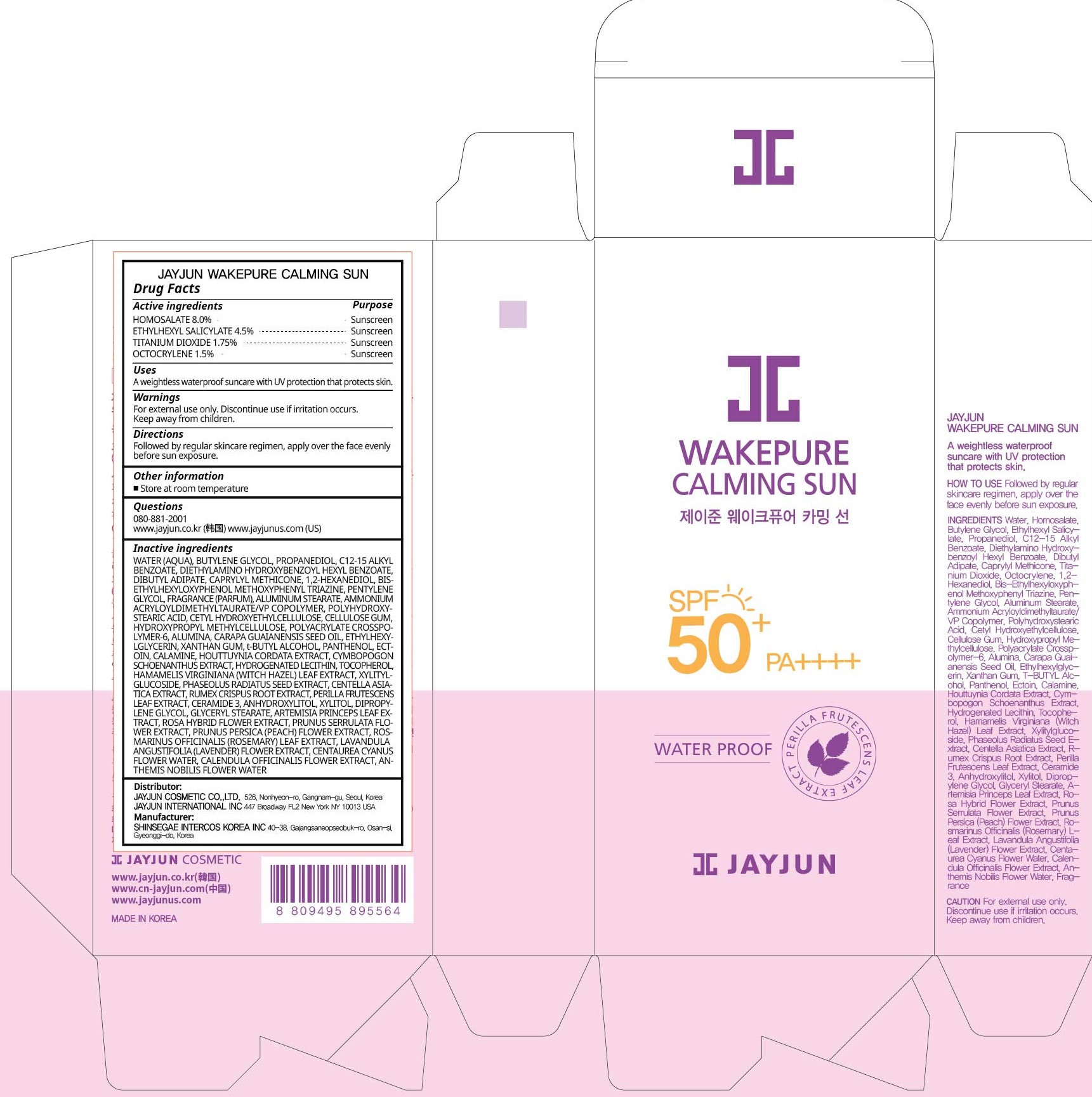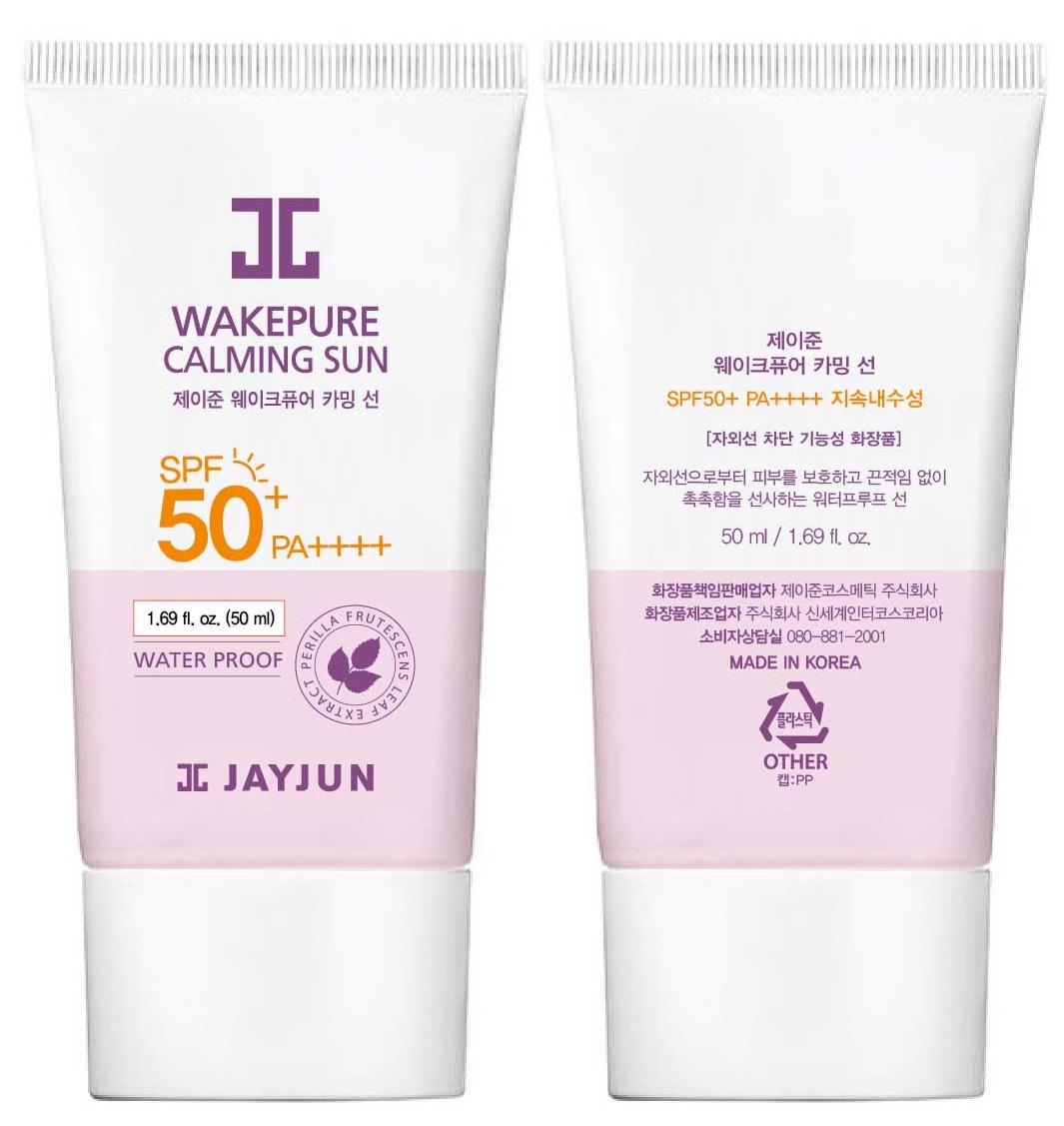 DRUG LABEL: JAYJUN WAKEPURE CALMING SUN
NDC: 70920-111 | Form: CREAM
Manufacturer: JAYJUN COSMETIC Co.,Ltd.
Category: otc | Type: HUMAN OTC DRUG LABEL
Date: 20200624

ACTIVE INGREDIENTS: HOMOSALATE 4.0 g/50 mL; OCTISALATE 2.25 g/50 mL; TITANIUM DIOXIDE 0.87 g/50 mL; OCTOCRYLENE 0.75 g/50 mL
INACTIVE INGREDIENTS: Water; BUTYLENE GLYCOL; PROPANEDIOL

ACTIVE INGREDIENTS

HOMOSALATE 8.0%
ETHYLHEXYL SALICYLATE 4.5%
TITANIUM DIOXIDE 1.75%
OCTOCRYLENE 1.5%

INACTIVE INGREDIENTS

WATER (AQUA), BUTYLENE GLYCOL, PROPANEDIOL, C12-15 ALKYL BENZOATE, DIETHYLAMINO HYDROXYBENZOYL HEXYL BENZOATE, DIBUTYL ADIPATE, CAPRYLYL METHICONE, 1,2-HEXANEDIOL, BIS-ETHYLHEXYLOXYPHENOL METHOXYPHENYL TRIAZINE,
PENTYLENE GLYCOL, FRAGRANCE (PARFUM), ALUMINUM STEARATE, AMMONIUM ACRYLOYLDIMETHYLTAURATE/VP COPOLYMER, POLYHYDROXYSTEARIC ACID, CETYL HYDROXYETHYLCELLULOSE, CELLULOSE GUM, HYDROXYPROPYL METHYLCELLULOSE,
POLYACRYLATE CROSSPOLYMER-6, ALUMINA, CARAPA GUAIANENSIS SEED OIL, ETHYLHEXYLGLYCERIN, XANTHAN GUM, t-BUTYL ALCOHOL, PANTHENOL, ECTOIN, CALAMINE, HOUTTUYNIA CORDATA EXTRACT, CYMBOPOGON SCHOENANTHUS EXTRACT,
HYDROGENATED LECITHIN, TOCOPHEROL, HAMAMELIS VIRGINIANA (WITCH HAZEL) LEAF EXTRACT, XYLITYLGLUCOSIDE, PHASEOLUS RADIATUS SEED EXTRACT, CENTELLA ASIATICA EXTRACT, RUMEX CRISPUS ROOT EXTRACT, PERILLA FRUTESCENS LEAF EXTRACT,
CERAMIDE 3, ANHYDROXYLITOL, XYLITOL, DIPROPYLENE GLYCOL, GLYCERYL STEARATE, ARTEMISIA PRINCEPS LEAF EXTRACT, ROSA HYBRID FLOWER EXTRACT, PRUNUS SERRULATA FLOWER EXTRACT, PRUNUS PERSICA (PEACH) FLOWER EXTRACT,
ROSMARINUS OFFICINALIS (ROSEMARY) LEAF EXTRACT, LAVANDULA ANGUSTIFOLIA (LAVENDER) FLOWER EXTRACT, CENTAUREA CYANUS FLOWER WATER, CALENDULA OFFICINALIS FLOWER EXTRACT, ANTHEMIS NOBILIS FLOWER WATER

PURPOSE

Sunscreen

WARNINGS

For external use only. Discontinue use if irritation occurs. Keep away from children.

DESCRIPTION

Uses:
A weightless waterproof suncare with UV protection that protects skin.

Directions:
Followed by regular skincare regimen, apply over the face evenly before sun exposure.

Other information

Store at room temperature

QUESTIONS

080-881-2001
www.jayjun.co.kr (韩国) www.jayjunus.com (US)